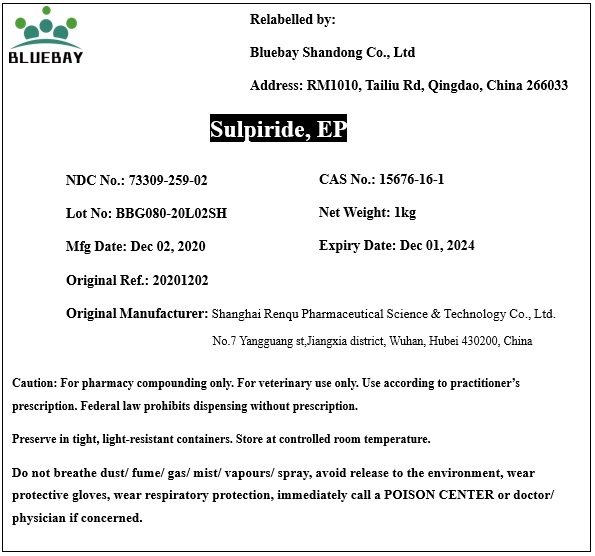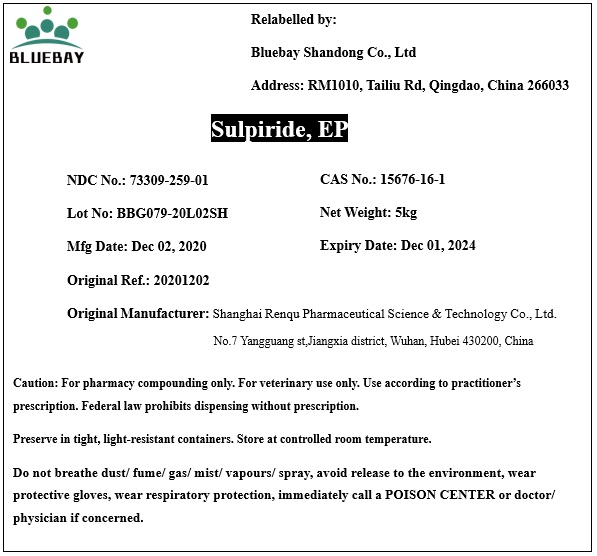 DRUG LABEL: Sulpiride
NDC: 73309-259 | Form: POWDER
Manufacturer: BLUEBAY SHANDONG CO.,LTD
Category: other | Type: BULK INGREDIENT
Date: 20210224

ACTIVE INGREDIENTS: SULPIRIDE 1 kg/1 kg

Sulpiride